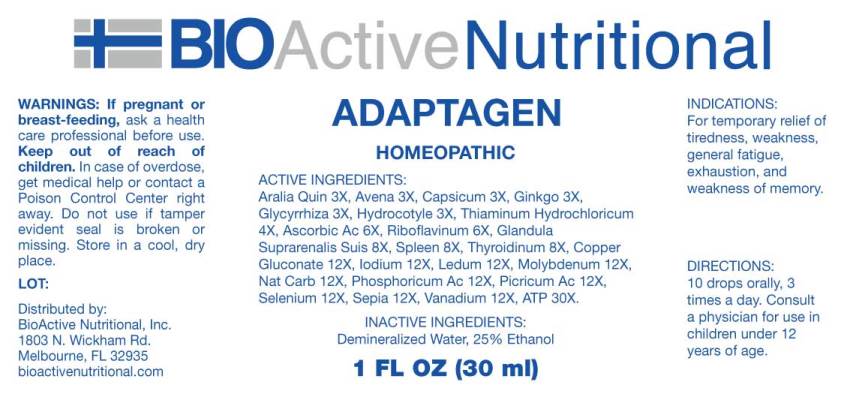 DRUG LABEL: Adaptagen
NDC: 43857-0506 | Form: LIQUID
Manufacturer: BioActive Nutritional, Inc.
Category: homeopathic | Type: HUMAN OTC DRUG LABEL
Date: 20241002

ACTIVE INGREDIENTS: AMERICAN GINSENG 3 [hp_X]/1 mL; AVENA SATIVA FLOWERING TOP 3 [hp_X]/1 mL; CAPSICUM 3 [hp_X]/1 mL; GINKGO 3 [hp_X]/1 mL; GLYCYRRHIZA GLABRA 3 [hp_X]/1 mL; CENTELLA ASIATICA WHOLE 3 [hp_X]/1 mL; THIAMINE HYDROCHLORIDE 4 [hp_X]/1 mL; ASCORBIC ACID 6 [hp_X]/1 mL; RIBOFLAVIN 6 [hp_X]/1 mL; SUS SCROFA ADRENAL GLAND 8 [hp_X]/1 mL; SUS SCROFA SPLEEN 8 [hp_X]/1 mL; THYROID 8 [hp_X]/1 mL; COPPER GLUCONATE 12 [hp_X]/1 mL; IODINE 12 [hp_X]/1 mL; LEDUM PALUSTRE TWIG 12 [hp_X]/1 mL; MOLYBDENUM 12 [hp_X]/1 mL; SODIUM CARBONATE 12 [hp_X]/1 mL; PHOSPHORIC ACID 12 [hp_X]/1 mL; PICRIC ACID 12 [hp_X]/1 mL; SELENIUM 12 [hp_X]/1 mL; SEPIA OFFICINALIS JUICE 12 [hp_X]/1 mL; VANADIUM 12 [hp_X]/1 mL; ADENOSINE TRIPHOSPHATE DISODIUM 30 [hp_X]/1 mL
INACTIVE INGREDIENTS: WATER; ALCOHOL

DRUG FACTS:

ACTIVE INGREDIENTS:

Aralia Quinquefolia 3X, Avena Sativa 3X, Capsicum Annuum 3X, Ginkgo Biloba 3X, Glycyrrhiza Glabra 3X, Hydrocotyle Asiatica 3X, Thiaminum Hydrochloricum 4X, Ascorbicum Acidum 6X, Riboflavinum 6X, Glandula Suprarenalis Suis 8X, Spleen (Suis) 8X, Thyroidinum (Suis) 8X, Cuprum Gluconate 12X, Iodium 12X, Ledum Palustre 12X, Molybdenum Metallicum 12X, Natrum Carbonicum 12X, Phosphoricum Acidum 12X, Picricum Acidum 12X, Selenium Metallicum 12X, Sepia 12X, Vanadium Metallicum 12X, Adenosinum Triphosphoricum Dinatrum 30X.

INDICATIONS:

For temporary relief of tiredness, weakness, general fatigue, exhaustion, and weakness of memory.

WARNINGS:

If pregnant or breast-feeding, ask a health care professional before use.

Keep out of reach of children. In case of overdose, get medical help or contact a Poison Control Center right away.

Do not use if tamper evident seal is broken or missing.

Store in cool, dry place.

Keep out of reach of children. In case of overdose, get medical help or contact a Poison Control Center right away.

DIRECTIONS:

10 drops orally, 3 times a day. Consult a physician for use in children under 12 years of age.

INDICATIONS:

For temporary relief of tiredness, weakness, general fatigue, exhaustion, and weakness of memory.

INACTIVE INGREDIENTS:

Demineralized Water, 25% Ethanol.

QUESTIONS:

Distributed by:
BioActive Nutritional, Inc.
1803 N. Wickham Rd.
Melbourne, FL 32935
bioactivenutritional.com

PACKAGE LABEL DISPLAY:

BIOActive Nutritional

ADAPTAGEN

HOMEOPATHIC

1 FL OZ (30 ml)